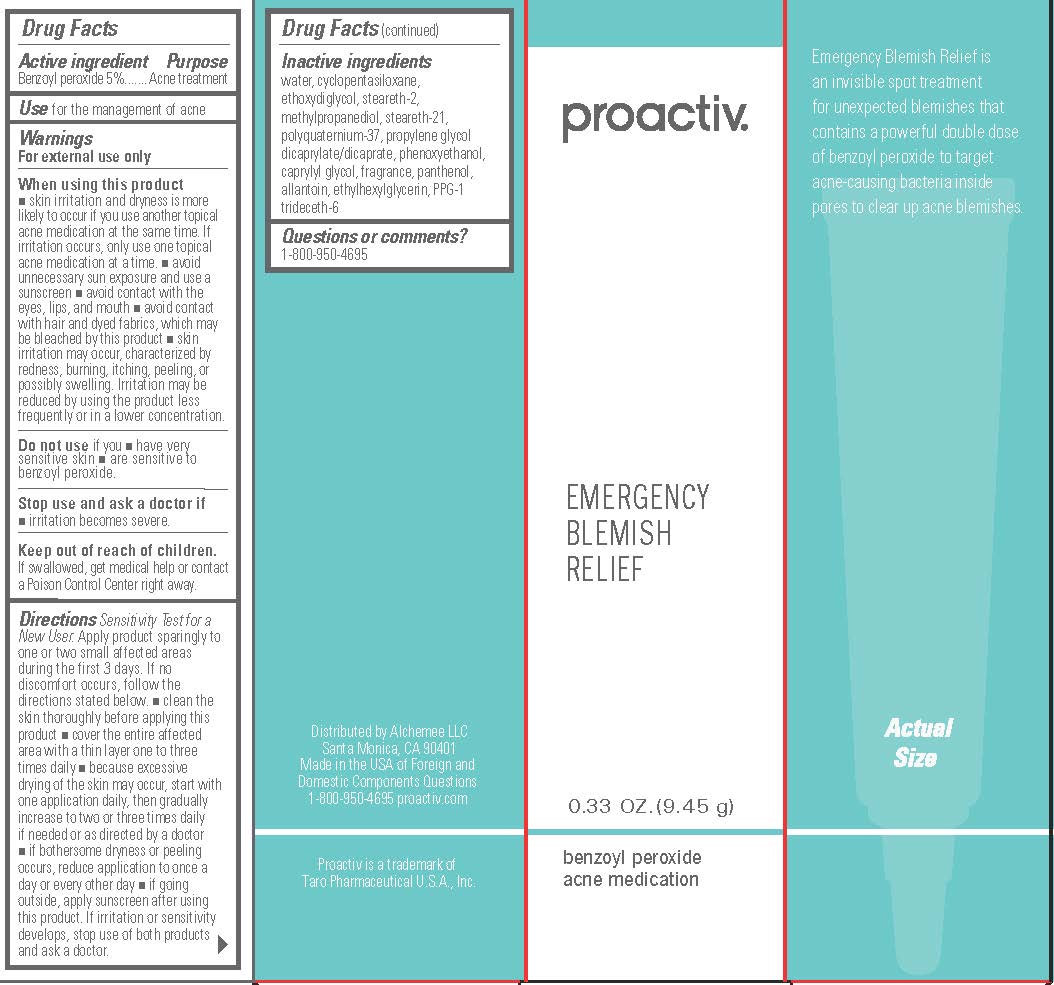 DRUG LABEL: Proactiv Emergency Blemish Relief
NDC: 11410-012 | Form: CREAM
Manufacturer: Alchemee, LLC
Category: otc | Type: HUMAN OTC DRUG LABEL
Date: 20260107

ACTIVE INGREDIENTS: BENZOYL PEROXIDE 5 g/100 g
INACTIVE INGREDIENTS: WATER; DIETHYLENE GLYCOL MONOETHYL ETHER; CYCLOMETHICONE 5; METHYLPROPANEDIOL; STEARETH-2; STEARETH-21; POLYQUATERNIUM-37 (3000 MPA.S); PROPYLENE GLYCOL DICAPRYLATE/DICAPRATE; PPG-1 TRIDECETH-6; PANTHENOL; ALLANTOIN; PHENOXYETHANOL; CAPRYLYL GLYCOL; ETHYLHEXYLGLYCERIN

Proactiv Emergency Blemish Relief

Drug Facts

Active ingredient

Benzoyl peroxide 5%

Purpose

Acne treatment

Use

for the management of acne

Warnings

For external use only

When using this product

- skin irritation and dryness is more likely to occur if you use another topical acne medication at the same time. If irritation occurs, only use one topical acne medication at a time.
- avoid unnecessary sun exposure and use a sunscreen
- avoid contact with the eyes, lips, and mouth
- avoid contact with hair and dyed fabrics, which may be bleached by this product
- skin irritation may occur, characterized by redness, burning, itching, peeling, or possibly swelling. Irritation may be reduced by using the product less frequently or in a lower concentration.

Do not useif you

- have very sensitive skin
- are sensitive to benzoyl peroxide.

Stop use and ask a doctor

- if irritation becomes severe.

Keep out of reach of children.

If swallowed, get medical help or contact a Poison Control Center right away.

Directions

- Sensitivity Test for a New User. Apply product sparingly to one or two small affected areas during the first 3 days. If no discomfort occurs, follow the directions stated below.
- clean the skin thoroughly before applying this product
- cover the entire affected area with a thin layer one to three times daily
- because excessive drying of the skin may occur, start with one application daily, then gradually increase to two or three times daily if needed or as directed by a doctor
- if bothersome dryness or peeling occurs, reduce application to once a day or every other day
- if going outside, apply sunscreen after using this product. If irritation or sensitivity develops, stop use of both products and ask a doctor.

Inactive ingredients

water, cyclopentasiloxane, ethoxydiglycol, steareth-2, methylpropanediol, steareth-21, polyquaternium-37, propylene glycol dicaprylate/dicaprate, phenoxyethanol, caprylyl glycol, fragrance, panthenol, allantoin, ethylhexylglycerin, PPG-1 trideceth-6

Questions or comments?

1-800-950-4695

Distributed by Alchemee LLC
Santa Monica, CA 90401
Made in the USA of Foreign and
Domestic Components Questions
1-800-950-4695 proactiv.com
Proactiv is a trademark of
Taro Pharmaceutical U.S.A., Inc.

PRINCIPAL DISPLAY PANEL - 9.45 g Tube Box

proactiv®

EMERGENCY
BLEMISH
RELIEF

0.33 OZ. (9.45 g)

benzoyl peroxide
acne medication